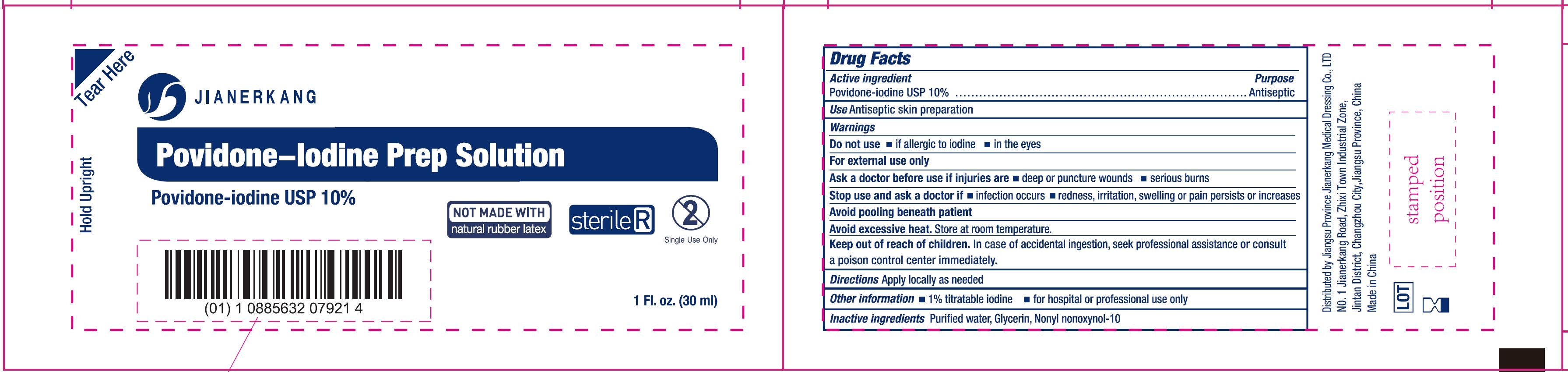 DRUG LABEL: Povidone Iodine Prep Solution Sterile
NDC: 34645-0013 | Form: SOLUTION
Manufacturer: Jianerkang Medical Co., Ltd
Category: otc | Type: HUMAN OTC DRUG LABEL
Date: 20231023

ACTIVE INGREDIENTS: POVIDONE-IODINE 100 mg/1 mL
INACTIVE INGREDIENTS: WATER; GLYCERIN

Povidone Iodine Prep Solution Sterile

Active ingredient

Povidone-iodine USP 10%

Purpose

Antiseptic

Use

Antiseptic skin preparation

Warnings

For external use only

Do not use

- if allergic to iodine
- in the eyes

Ask a doctor before use if injuries are

- deep or puncture wounds
- serious burns

Stop use and ask a doctor if

- infection occurs
- redness, irritation, swelling or pain persists or increases

Store at room temperature. Avoid pooling beneath patient Avoid excessive heat.

Keep out of reach of children.

In case of accidental ingestion, seek professinoal assistance or consult a poion control center immediately

Directions

Apply locally as needed

Other information

- 1% titratable iodine
- for hospital or professional use only

Inactive ingredients

Purified water, Glycerin, Nonyl nonoxynol-10